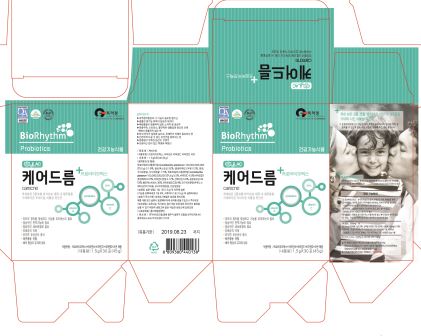 DRUG LABEL: CARECNE
NDC: 72339-0001 | Form: POWDER
Manufacturer: Biorhythm Co., LTD
Category: otc | Type: HUMAN OTC DRUG LABEL
Date: 20180522

ACTIVE INGREDIENTS: LACTOBACILLUS PLANTARUM 51.9 g/100 g
INACTIVE INGREDIENTS: MALTODEXTRIN; POLYDEXTROSE

ACTIVE INGREDIENT

lactobacillus plantarum

INACTIVE INGREDIENT

polydextrose, maltodextrin, corn starch, etc

PURPOSE

Kimchi Lactobacillus is made to induce the proliferation of intestinal-beneficial bacteria, the inhibition of harmful bacteria and regular bowel movements, and to help immunity by intestinal absorption and normal cell division. It helps to improve eye health.

Lactobacillus plantarum K-1 probiotics also relieve and reduce constipation, enteritis, rhinitis, vaginitis, atopic dermatitis, acne, liver spots, and freckles. Biorhythm guarantees quality and satisfaction.

WARNINGS

Keep out of reach of infants and children
Do not to store in a place with high/low temperature and exposed to direct sunlight

Keep out of reach of children.

INDICATIONS AND USAGE

take 1.5g per day

DOSAGE AND ADMINISTRATION

for oral use only